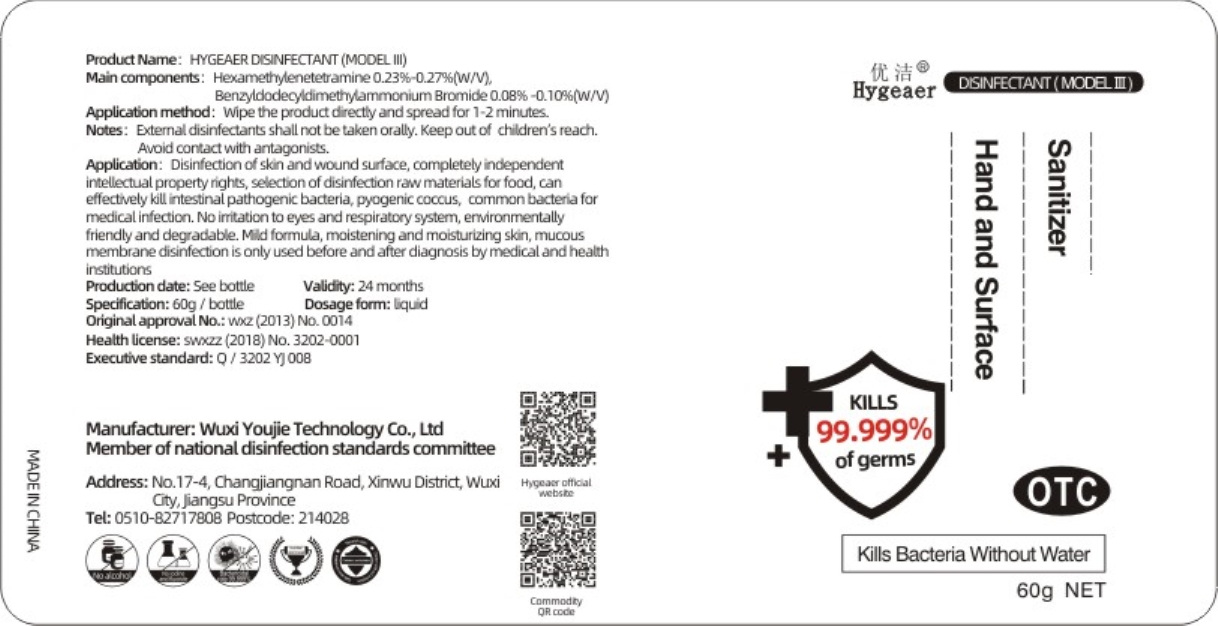 DRUG LABEL: Disinfectant(Model III)Sanitizer Hand And Surface
NDC: 54796-005 | Form: LIQUID
Manufacturer: Wuxi Youjie Technology Co. LTD
Category: otc | Type: HUMAN OTC DRUG LABEL
Date: 20200428

ACTIVE INGREDIENTS: METHENAMINE 0.15 g/60 g; BENZALKONIUM BROMIDE 0.054 g/60 g
INACTIVE INGREDIENTS: WATER

DOSAGE AND ADMINISTRATION

Don't put it in a damp place.

INACTIVE INGREDIENT

water

INDICATIONS AND USAGE

Wipe the product directly and spread for 1-2 minutes.

ACTIVE INGREDIENT

HEXAMETHYLENETETRAMINE

BENZALKONIUM BROMIDE

keep out of reach of children

PURPOSE

Disinfection
Sterilization

WARNINGS

Extemnal disinfectants shall not be taken orally. Keep out of children's reach.Avolid contact with antagonists.